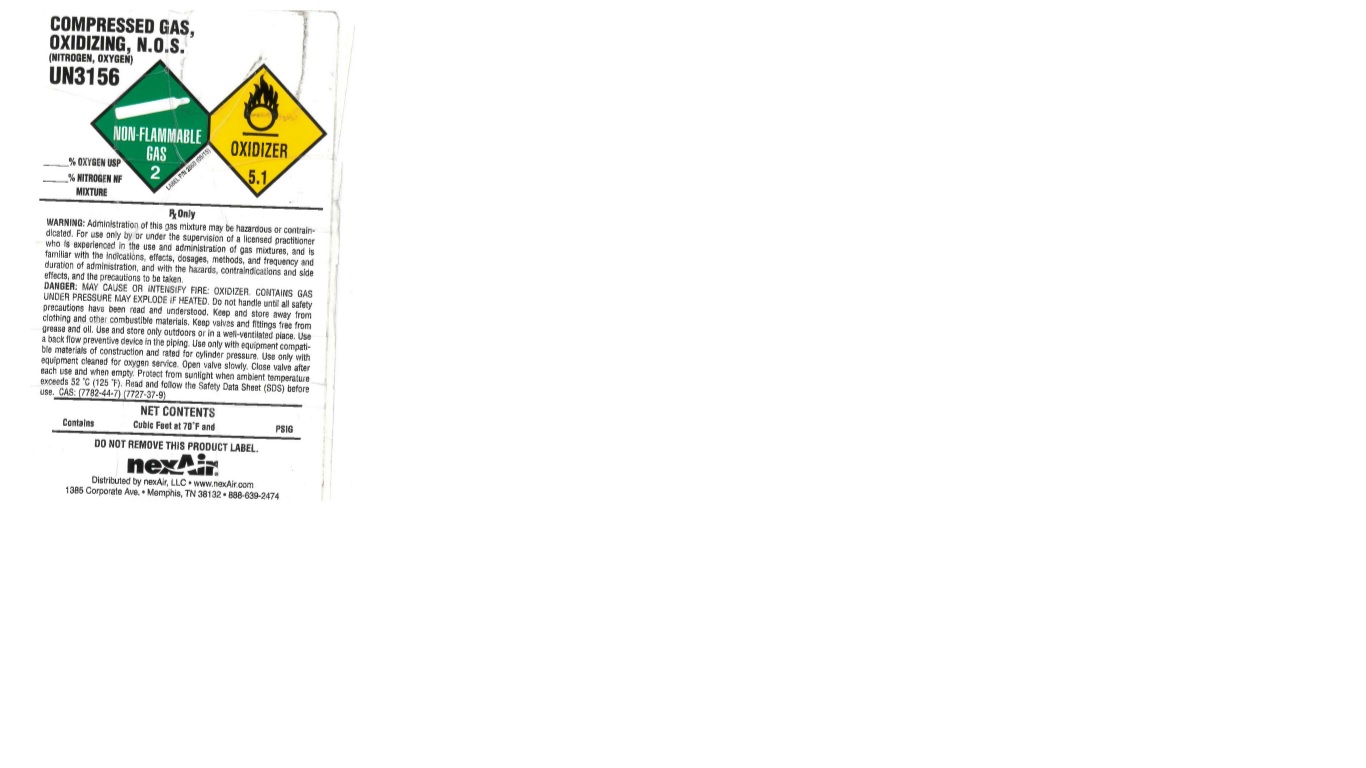 DRUG LABEL: 40% Oxygen/Nitrogen Mix
NDC: 12213-200 | Form: GAS
Manufacturer: NexAir LLC
Category: prescription | Type: HUMAN PRESCRIPTION DRUG LABEL
Date: 20251031

ACTIVE INGREDIENTS: OXYGEN 400 mL/1 L
INACTIVE INGREDIENTS: NITROGEN 600 mL/1 L

40% Oxygen/ Nitrogen Mix

PACKAGE LABEL

COMPRESSED GAS, OXIDIZING, N.O.S. (NITROGEN, OXYGEN)

UN3156

% OXYGEN USP

% NITROGEN NF MIXTURE

RX ONLY

WARNING: Administration of this gas mixture may be hazardous or contraindicated. For use only by or under the supervision of a licensed practitioner who is experienced in the use and administration of gas mixtures, and is familiar with the indications, effects, dosages, methods, and frequency and duration of administration, and with the hazards, contraindications and side effects, and the precautions to be taken.

DANGER: MAY CAUSE OR INTENSIFY FIRE: OXIDIZER. CONTAINS GAS UNDER PRESSURE MAY EXPLODE IF HEATED. Do not handle until all safety precautions have been read and understood. Keep and store away from clothing and other combustible materials. Keep valves and fittings free from grease and oil. Use and store only outdoors or in a well-ventilated place. Use a back flow preventive device in the piping. Use only equipment compatible materials of construction and rated for cylinder pressure. Use only with equipment cleaned for oxygen service. Open valve slowly. Close valve after each use and when empty. Protect from sunlight when ambient temperature exceeds 52 C (125 F). Read and follow the Safety Data Sheet (SDS) before use. CAS: (7782-44-7) (7727-37-9)

NET CONTENTS

Contains Cubic Feet at 70 F and PSIG

DO NOT REMOVE THIS PRODUCT LABEL.

nexAir

Distributed by nexAir, LLC www.nexair.com

1385 Corporate Ave. Memphis, TN 38132 888-639-2474